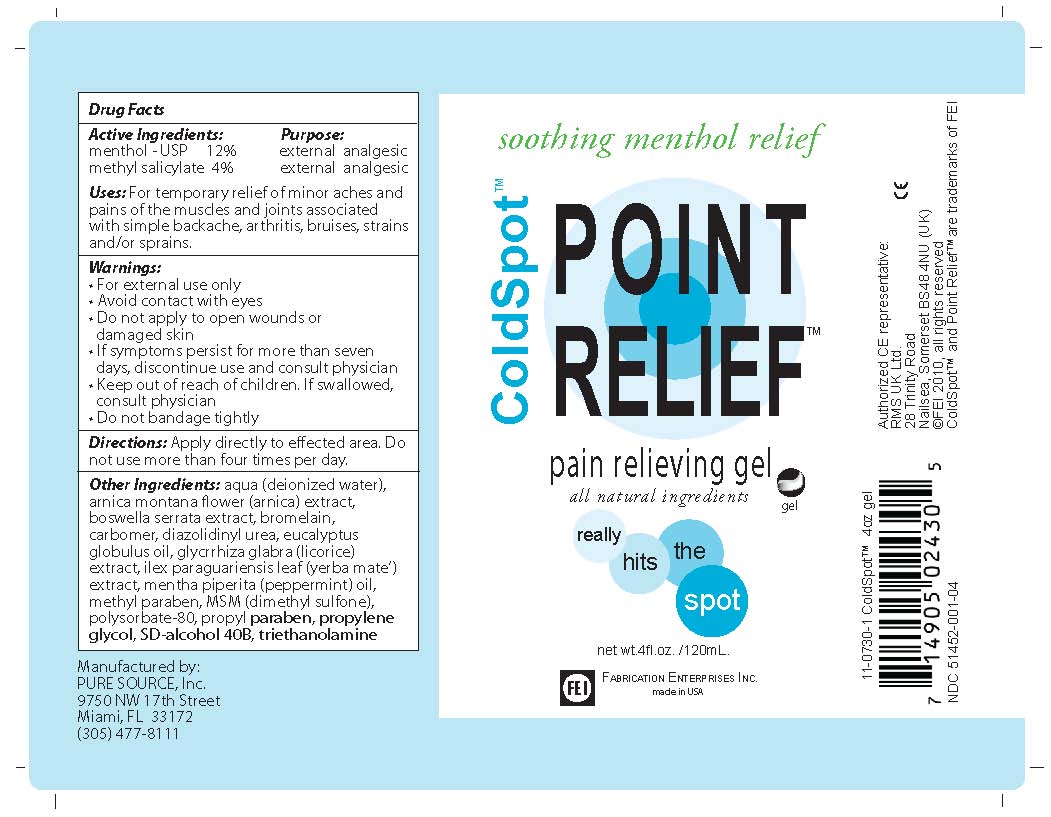 DRUG LABEL: Cold Spot
NDC: 65121-001 | Form: GEL
Manufacturer: Pure Source
Category: otc | Type: HUMAN OTC DRUG LABEL
Date: 20100828

ACTIVE INGREDIENTS: Menthol 14 mL/120 mL; METHYL SALICYLATE 5 mL/120 mL
INACTIVE INGREDIENTS: water; Arnica cordifolia flower; Chondroitin sulfate (bovine); Citric Acid; Eucalyptus Globulus leaf; Glucosamine sulfate; ILEX PARAGUARIENSIS LEAF; Isopropyl Alcohol; Peppermint Oil; Dimethyl Sulfone; polysorbate 20; alcohol

Cold Spot Point Relief Pain relieving Spray - 4 oz. gel

Active ingredients: MENTHOL, METHYL SALICYLATE

INACTIVE INGREDIENT

Inactive Ingredients: deionized water, arnica, chondroitin sulfate, citirc acid, euclayptus oil, glucosamine sulfate, ilex paraguariesis leaf, isopropyl alcohol, peppermint oil, dimethyl sulfone, polysorbate-20, SD alcohol 40B.

Keep out of reach of children. If swallowed consult physician

WARNINGS

Warnings Section: For external use only, avoid contact with eyes, do not apply to open wounds or damaged skin, if symptoms persist for more than seven days discontinue use and consult physician, keep out of reach of children and if swallowed consult physician, do not bandage tightly.

PURPOSE

Use: For temporary relief of minor aches and pains of the muscles and joints associated with simple backache, arthritis, bruises, strains and/or sprains.

INDICATIONS AND USAGE

For temporary relief of minor aches and pains of the muscles and joints associated with simple backache, arthritis, bruises, strains and/or sprains.

DOSAGE AND ADMINISTRATION

Apply directly to effected area. Do not use more than four times per day.

PACKAGE LABEL

Cold Point Relief pain relieving spray. All natural ingredients